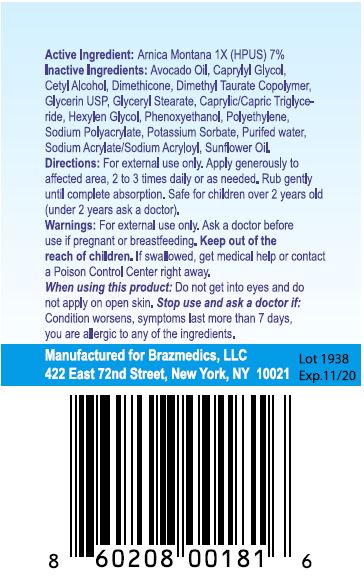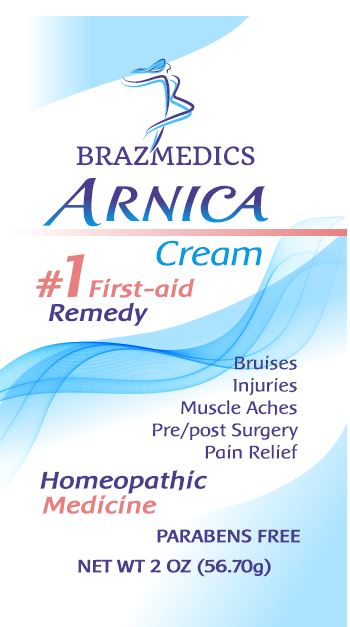 DRUG LABEL: BRAZMEDICS ARNICA Cream
NDC: 61727-114 | Form: CREAM
Manufacturer: Homeocare Laboratories
Category: homeopathic | Type: HUMAN OTC DRUG LABEL
Date: 20260112

ACTIVE INGREDIENTS: ARNICA MONTANA 1 [hp_X]/1 [hp_X]
INACTIVE INGREDIENTS: AVOCADO OIL; DIMETHICONE; SODIUM ACRYLATE/SODIUM ACRYLOYLDIMETHYLTAURATE COPOLYMER (4000000 MW); TRICAPRIN; HEXYLENE GLYCOL; GLYCERYL MONOSTEARATE; GLYCERIN; HIGH DENSITY POLYETHYLENE; CAPRYLYL GLYCOL; CETYL ALCOHOL; PHENOXYETHANOL; SODIUM POLYACRYLATE (2500000 MW); POTASSIUM SORBATE; WATER; SODIUM ACRYLATE; SUNFLOWER OIL

BRAZMEDICS ARNICA Cream

Active Ingredient:

Arnica Montana 1X (HPUS) 7%

Purpose

#1 First-aid Remedy for the relief of Bruises, Injuries, Muscle Aches, Pre/Post Surgery, Pain Relief

Homeopathic Medicine

PARABENS FREE

Keep out of the reach of children. If swallowed, get medical help or contact a Poison Control Center right away.

Warnings:

For external use only. Ask a doctor before use if pregnant or breastfeeding. Keep out of the reach of children. If swallowed, get medical help or contact a Poison Control Center right away.

Inactive Ingredients:

Avocado Oil, Caprylyl Glycol, Cetyl Alcohol, Dimethicone, Dimethyl Taurate Copolymer, Glycerin USP, Glyceryl Stearate, Caprylic/Capric Triglyceride, Hexylen Glycol, Phenoxyethanol, Polyethylene, Sodium Polyacrylate, Potassium Sorbate, Purified water, Sodium Acrylate/Sodium Acryloyl, Sunflower Oil

Directions:

For external use only. Apply generously to affected area, 2 to 3 times daily or as needed. Rub gently until complete absorption. Safe for children over 2 year old (under 2 years ask a doctor).

When using this product: Do not get into eyes and do not apply on open skin. Stop use and ask a doctor if: Condition worsens, symptoms last more than 7 days, you are allergic to any of the ingredients.

Directions:

For external use only. Apply generously to affected area, 2 to 3 times daily or as needed. Rub gently until complete absorption. Safe for children over 2 years old (under 2 years ask a doctor).